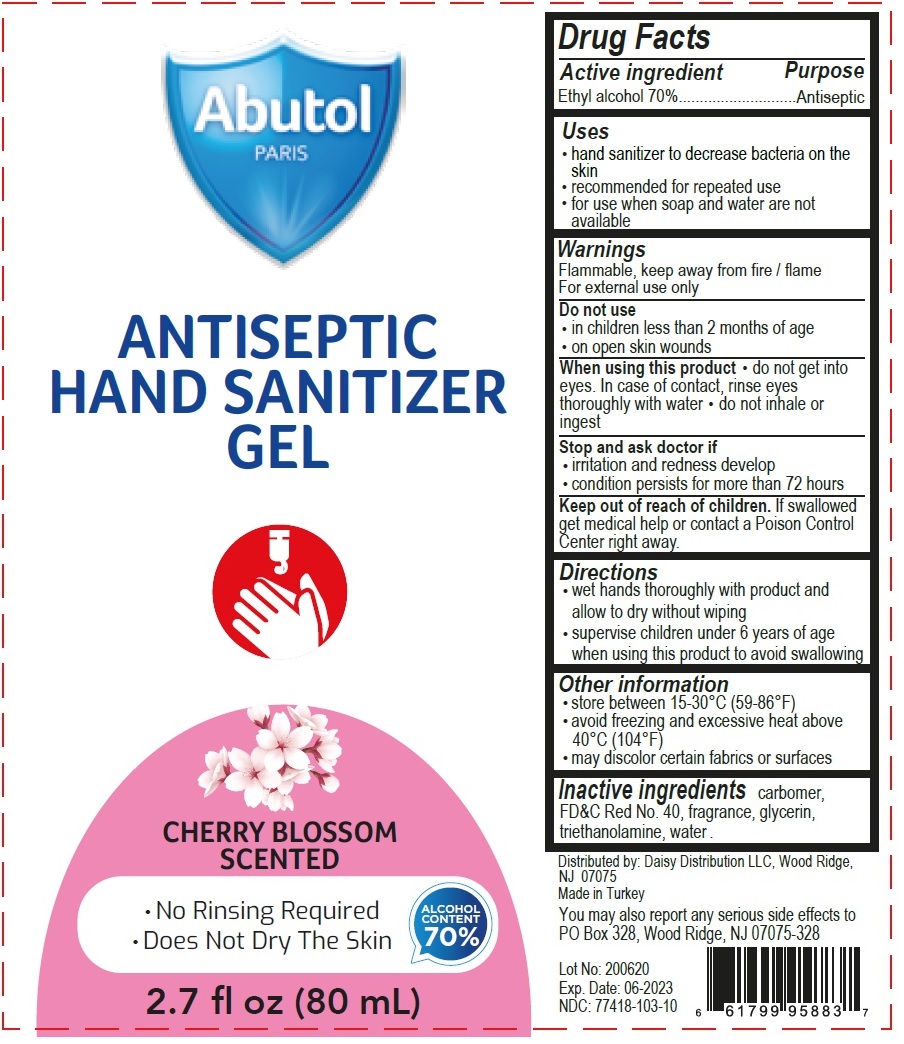 DRUG LABEL: Abutol PARIS ANTISEPTIC HAND SANITIZER
NDC: 77418-103 | Form: GEL
Manufacturer: ATAK FARMA KOZMETIK VE KIMYA SANAYI TICARET ANONIM SIRKETI
Category: otc | Type: HUMAN OTC DRUG LABEL
Date: 20200604

ACTIVE INGREDIENTS: ALCOHOL 70 mL/100 mL
INACTIVE INGREDIENTS: CARBOMER HOMOPOLYMER, UNSPECIFIED TYPE; FD&C Red No. 40; GLYCERIN; TROLAMINE; WATER

Abutol PARIS ANTISEPTIC HAND SANITIZER GEL CHERRY BLOSSOM SCENTED

Active ingredient

Ethyl alcohol 70%

Purpose

Antiseptic

Uses

• hand sanitizer to decrease bacteria on the skin
• recommended for repeated use
• for use when soap and water are not available

Warnings

Flammable, keep away from fire / flame
For external use only

Do not use• in children less than 2 months of age
• on open skin wounds
When using this product • do not get into eyes. In case of contact, rinse eyes thoroughly with water. • Do not inhale or ingest.

Stop and ask doctor if
• irritation and redness develop
• condition persists for more than 72 hours

Keep out of reach of children.

If swallowed get medical help or contact a Poison Control Center right away.

Directions

• wet hands thoroughly with product and allow to dry without wiping
• supervise children under 6 years of age when using this product to avoid swallowing

Other information

• store between 15-30°C (59-86°F)
• avoid freezing and excessive heat above 40°C (104°F)
• may discolor certain fabrics or surfaces

INACTIVE INGREDIENT

carbomer, FD&C Red No.40, fragrance, glycerin, triethanolamine, water.

Distributed by: Daisy Distribution LLC, Wood Ridge, NJ 07075
Country Of Origin: Turkey

You may also report any serious side effects to
PO Box 328, Wood Ridge, NJ 07075-328

Lot No: 200620
Exp. Date: 06-2023
NDC: 77418-103-10

661799958837

•No Rinsing Required
•Does Not Dry The Skin

ALCOHOL CONTENT 70%